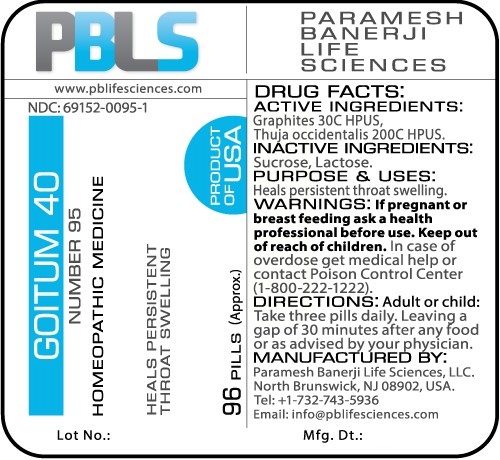 DRUG LABEL: Goitum 40 Number 95
NDC: 69152-0095 | Form: PELLET
Manufacturer: Paramesh Banerji Life Sciences LLC
Category: homeopathic | Type: HUMAN OTC DRUG LABEL
Date: 20161109

ACTIVE INGREDIENTS: THUJA OCCIDENTALIS LEAFY TWIG 200 [hp_C]/1 1; GRAPHITE 30 [hp_C]/1 1
INACTIVE INGREDIENTS: SUCROSE; LACTOSE

DRUG FACTS: Active Ingredients

Graphites 30C HPUS, Thuja occidentalis 200C HPUS

Inactive Ingredients

Sucrose, Lactose

Purpose

Heals persistent throat swelling

Uses

Heals persistent throat swelling

Warnings

If pregnant or breast feeding ask a health professional before use.

Keep out of reach of children. In case of overdose, get medical help or contact a Poison Control Center (1-800-222-1222) right away.

Direction

Adult or child: Take three pills daily. Leaving a gap of 30 minutes after any food or as advised by your physician.

Manufactured by

Paramesh Banerji Life Sciences, LLC.

North Brunswick, NJ 08902, USA.

Tel: +1-732-743-5936

Email: info@pblifesciences.com

Principal Display Panel

NDC: 69152-0095-1

Goitum 40

Number 95

Homeopathic Medicine

Graphites 30C HPUS, Thuja occidentalis 200C HPUS

Heals persistent throat swelling

96 Pills (Approx.)

Product of USA